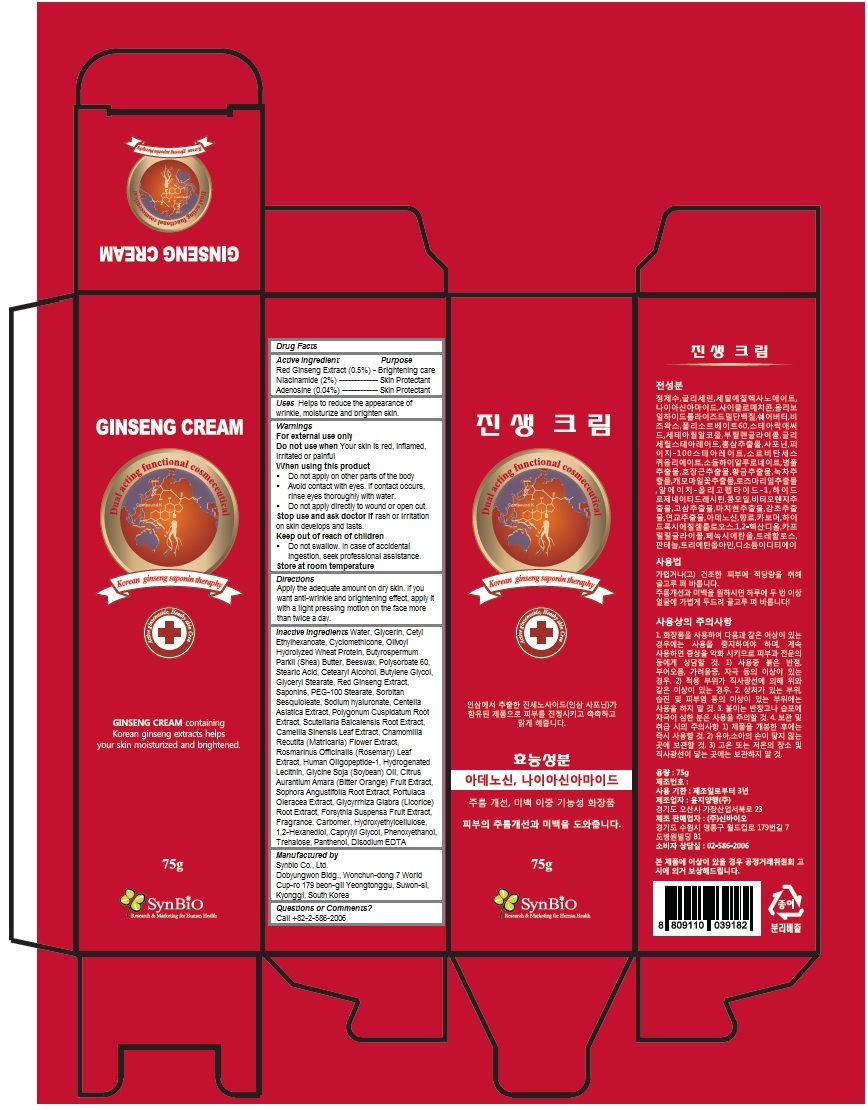 DRUG LABEL: Ginseng
NDC: 70969-100 | Form: CREAM
Manufacturer: Synbio Co., Ltd.
Category: otc | Type: HUMAN OTC DRUG LABEL
Date: 20160914

ACTIVE INGREDIENTS: Niacinamide 1.5 g/75 g; Adenosine 0.03 g/75 g
INACTIVE INGREDIENTS: water; glycerin; CETYL ETHYLHEXANOATE; CYCLOMETHICONE; SHEA BUTTER; YELLOW WAX; POLYSORBATE 60; STEARIC ACID; CETOSTEARYL ALCOHOL; Butylene Glycol; GLYCERYL MONOSTEARATE; PEG-100 STEARATE; SORBITAN SESQUIOLEATE; HYALURONATE SODIUM; CENTELLA ASIATICA; POLYGONUM CUSPIDATUM ROOT; SCUTELLARIA BAICALENSIS ROOT; GREEN TEA LEAF; CHAMOMILE; ROSEMARY; HYDROGENATED SOYBEAN LECITHIN; SOYBEAN OIL; CITRUS AURANTIUM FRUIT OIL; SOPHORA FLAVESCENS ROOT; PURSLANE; GLYCYRRHIZA GLABRA; FORSYTHIA SUSPENSA FRUIT; CARBOXYPOLYMETHYLENE; HYDROXYETHYL CELLULOSE (100 MPA.S AT 2%); 1,2-HEXANEDIOL; CAPRYLYL GLYCOL; PHENOXYETHANOL; TREHALOSE; Panthenol; EDETATE DISODIUM ANHYDROUS; ASIAN GINSENG

Ginseng Cream

Active Ingredients

Niacinamide (2%)

Adenosine (0.04%)

Purpose

Skin Protectant

Keep out of reach of children

Do not swallow. In case of accidental ingestion, seek professional assistance.

Uses

Helps to reduce the appearance of wrinkle, moisturize and brighten skin.

Warnings

For external use only
Do not use when Your skin is red, inflamed, irritated or painful
When using this product
- Do not apply on other parts of the body
- Avoid contact with eyes. If contact occurs, rinse eyes thoroughly with water.
- Do not apply directly to wound or open cut.
Stop use and ask doctor if rash or irritation on skin develops and lasts.

Store at room temperature

Directions

Apply the adequate amount on a dried and itching skin. If you want anti-wrinkle and brightening effect, apply it with a light pressing motion on the face more than twice a day.

Inactive Ingredients

Water, Glycerin, Cetyl Ethylhexanoate, Cyclomethicone, Olivoyl Hydrolyzed Wheat Protein, Butyrospermum Parkii (Shea) Butter, Beeswax, Polysorbate 60, Stearic Acid, Cetearyl Alcohol, Butylene Glycol, Glyceryl Stearate, Red Ginseng Extract, Saponins, PEG-100 Stearate, Sorbitan Sesquioleate, Sodium hyaluronate, Centella Asiatica Extract, Polygonum Cuspidatum Root Extract, Scutellaria Baicalensis Root Extract, Camellia Sinensis Leaf Extract, Chamomilla Recutita (Matricaria) Flower Extract, Rosmarinus Officinalis (Rosemary) Leaf Extract, Human Oligopeptide-1, Hydrogenated Lecithin, Glycine Soja (Soybean) Oil, Citrus Aurantium Amara (Bitter Orange) Fruit Extract, Sophora Angustifolia Root Extract, Portulaca Oleracea Extract, Glycyrrhiza Glabra (Licorice) Root Extract, Forsythia Suspensa Fruit Extract, Fragrance, Carbomer, Hydroxyethylcellulose, 1,2-Hexanediol, Caprylyl Glycol, Phenoxyethanol, Trehalose, Panthenol, Disodium EDTA